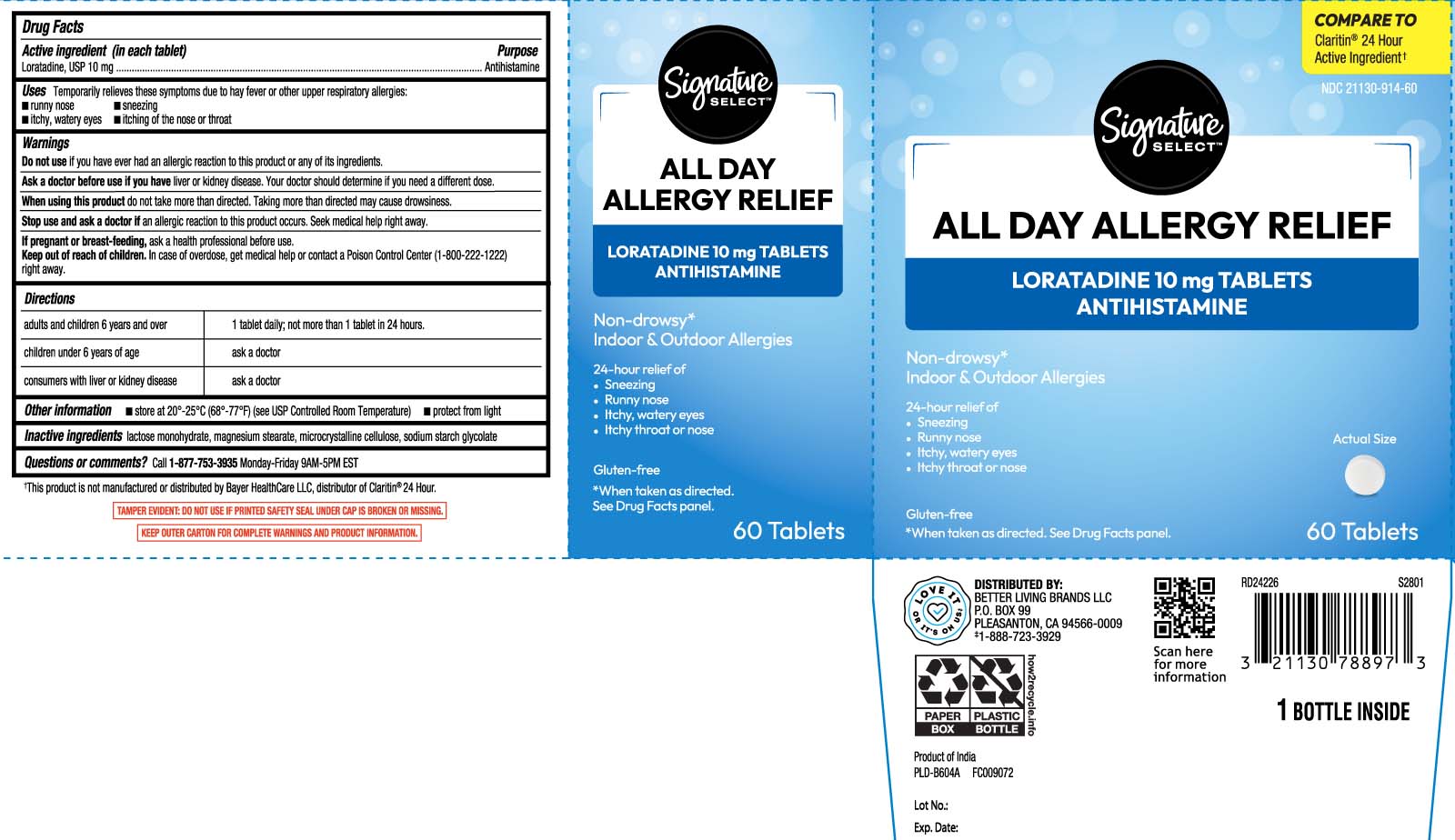 DRUG LABEL: All Day Allergy Relief
NDC: 21130-914 | Form: TABLET
Manufacturer: Safeway, Inc.
Category: otc | Type: HUMAN OTC DRUG LABEL
Date: 20260105

ACTIVE INGREDIENTS: LORATADINE 10 mg/1 1
INACTIVE INGREDIENTS: LACTOSE MONOHYDRATE; MAGNESIUM STEARATE; MICROCRYSTALLINE CELLULOSE; SODIUM STARCH GLYCOLATE TYPE A CORN

Drug Facts

Active ingredient (in each tablet)

Loratadine, USP 10 mg

Purpose

Antihistamine

Uses

temporarily relieves these symptoms due to hay fever or other upper respiratory allergies:

- runny nose
- sneezing
- itchy, watery eyes
- itching of the nose or throat

Warnings

Do not use

if you have ever had an allergic reaction to this product or any of its ingredients.

Ask a doctor before use if you have

liver or kidney disease. Your doctor should determine if you need a different dose.

When using this product

do not take more than directed. Taking more than directed may cause drowsiness.

Stop use and ask a doctor if

an allergic reaction to this product occurs. Seek medical help right away.

If pregnant or breast-feeding,

ask a health professional before use.

Keep out of reach of children.

In case of overdose, get medical help or contact a Poison Control Center (1-800-222-1222) right away.

Directions

adults and children 6 years and over | 1 tablet daily; not more than 1 tablet in 24 hours
children under 6 years of age | ask a doctor
consumers with liver or kidney disease | ask a doctor

Other information

- store at 20º-25ºC (68º-77ºF) (see UPS Controlled Room Temperature)
- protect from light

Inactive ingredients

lactose monohydrate, magnesium stearate, microcrystalline cellulose, sodium starch glycolate

Questions or comments?

Call 1-877-753-3935 Monday-Friday 9AM-5PM EST

Principal Display Panel

COMPARE TO Claritin® 24 Hour active ingredient†

All Day Allergy Relief

LORATADINE TABLETS, 10mg

Antihistamine

Non-Drowsy*

Indoor & Outdoor Allergies

24 hour relief of:

- Sneezing
- Runny Nose
- Itchy, watery eyes
- Itchy Throat or Nose

Gluten-free

TABLETS

*When taken as directed. See Drug Facts panel.

*This product is not manufactured or distributed by Bayer Healthcare LLC, distributor of Claritin® 24 Hour.

TAMPER EVIDENT: DO NOT USE IF PRINTED SAFETY SEAL UNDER CAP IS BROKEN OR MISSING.

KEEP OUTER CARTON FOR COMPLETE WARNINGS AND PRODUCT INFORMATION.

DISTRIBUTED BY:

BETTER LIVING BRANDS LLC

P.O. BOX 99, PLEASANTON, CA 94566-0009

Package Label

SIGNATURE SELECT All Day Allergy Relief